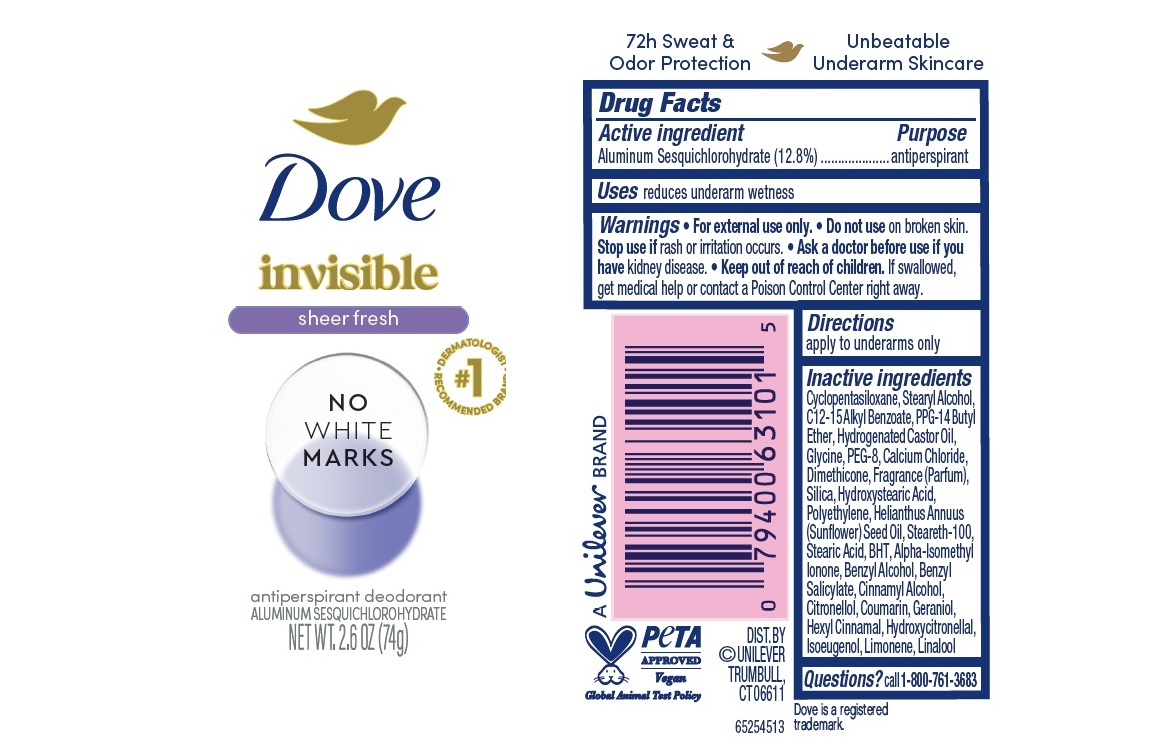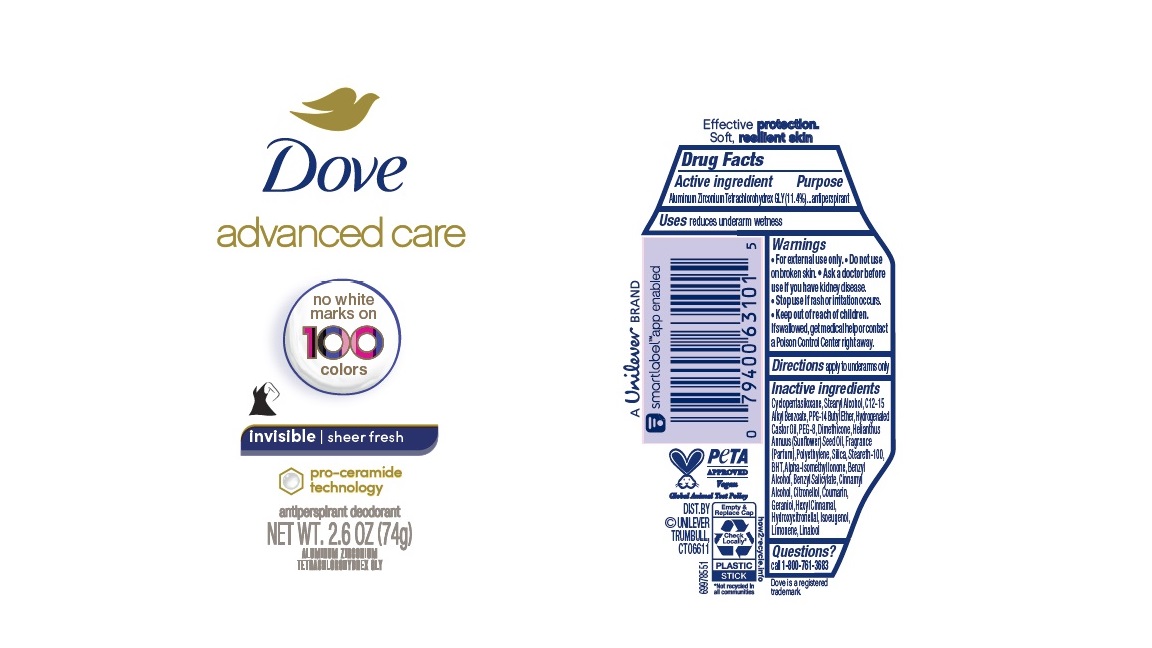 DRUG LABEL: Dove
NDC: 64942-2247 | Form: STICK
Manufacturer: Conopco Inc. d/b/a/ Unilever
Category: otc | Type: HUMAN OTC DRUG LABEL
Date: 20260220

ACTIVE INGREDIENTS: ALUMINUM ZIRCONIUM TETRACHLOROHYDREX GLY 11.4 g/100 g
INACTIVE INGREDIENTS: .ALPHA.-HEXYLCINNAMALDEHYDE; .ALPHA.-AMYLCINNAMALDEHYDE; HYDROXYCITRONELLAL; STEARYL ALCOHOL; CYCLOMETHICONE 5; ISOEUGENOL; GERANIOL; HYDROGENATED CASTOR OIL; HIGH DENSITY POLYETHYLENE; BUTYLATED HYDROXYTOLUENE; PPG-14 BUTYL ETHER; SUNFLOWER OIL; SILICON DIOXIDE; ALKYL (C12-15) BENZOATE; DIMETHICONE; STEARETH-100; POLYETHYLENE GLYCOL 400; .BETA.-CITRONELLOL, (R)-; ISOMETHYL-.ALPHA.-IONONE; LIMONENE, (+)-; BENZYL ALCOHOL; BENZYL SALICYLATE; COUMARIN; LINALOOL, (+/-)-

Dove Advanced Care Invisible Sheer Fresh Antiperspirant Deodorant

Drug Facts

Active ingredient

Aluminum Zirconium Tetrachlorohydrex GLY (11.4 %)

Purpose

antiperspirant

Uses

• reduces underarm wetness

Warnings

• For external use only.
• Do not use on broken skin .
• Ask a doctor before use if you have kidney disease.
• Stop use if rash or irritation occurs.

• Keep out of reach of children.

If swallowed, get medical help or contact a Poison Control Center right away.

Directions

apply to underarms only

Inactive ingredients

Cyclopentasiloxane, Stearyl Alcohol, C12-15 Alkyl Benzoate, PPG-14 Butyl Ether, Hydrogenated Castor Oil, PEG-8, Dimethicone, Helianthus Annuus (Sunflower) Seed Oil, Fragrance (Parfum), Polyethylene, Silica, Steareth-100, BHT, Alpha-Isomethyl Ionone, Benzyl Alcohol, Benzyl Salicylate, Cinnamyl Alcohol, Citronellol, Coumarin, Geraniol, Hexyl Cinnamal, Hydroxycitronellal, Isoeugenol, Limonene, Linalool

Questions?

Call 1-800-761-3683